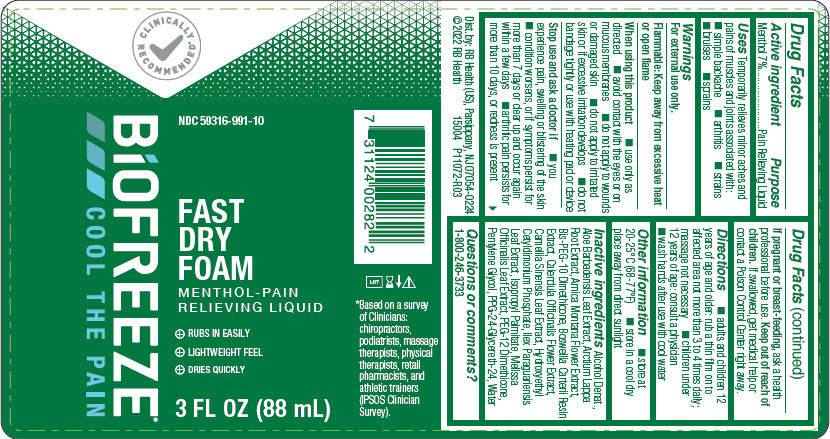 DRUG LABEL: Biofreeze Foam
NDC: 59316-991 | Form: LIQUID
Manufacturer: RB Health (US) LLC
Category: otc | Type: HUMAN OTC DRUG LABEL
Date: 20241227

ACTIVE INGREDIENTS: MENTHOL, UNSPECIFIED FORM 70 mg/1 mL
INACTIVE INGREDIENTS: ALCOHOL; ALOE VERA LEAF; ARCTIUM LAPPA ROOT; ARNICA MONTANA FLOWER; BIS-PEG-10 DIMETHICONE/DIMER DILINOLEATE COPOLYMER; FRANKINCENSE; CALENDULA OFFICINALIS FLOWER; GREEN TEA LEAF; HYDROXYETHYL CETYLDIMONIUM PHOSPHATE; ILEX PARAGUARIENSIS LEAF; ISOPROPYL PALMITATE; MELISSA OFFICINALIS LEAF; PEG-12 DIMETHICONE (300 CST); PENTYLENE GLYCOL; PPG-24-GLYCERETH-24; WATER

Biofreeze®Foam

Drug Facts

Active ingredient

Menthol 7%

Purpose

Pain Relieving Liquid

Uses

Temporarily relieves minor aches and pains of muscles and joints associated with:

- simple backache
- arthritis
- strains
- bruises
- sprains

Warnings

For external use only.

Flammable: Keep away from excessive heat or open flame

When using this product

- use only as directed
- avoid contact with the eyes or on mucous membranes
- do not apply to wounds or damaged skin
- do not apply to irritated skin or if excessive irritation develops
- do not bandage tightly or use with heating pad or device

Stop use and ask a doctor if

- you experience pain, swelling or blistering of the skin
- condition worsens, or if symptoms persist for more than 7 days or clear up and occur again within a few days
- arthritic pain persists for more than 10 days, or redness is present

PREGNANCY OR BREAST FEEDING

If pregnant or breast-feeding,ask a health professional before use.

Keep out of reach of children.If swallowed, get medical help or contact a Poison Control Center right away.

Directions

- adults and children 12 years of age and older: rub a thin film on to affected area not more than 3 to 4 times daily; massage not necessary
- children under 12 years of age: consult a physician
- wash hands after use with cool water

Other information

- store at 20-25°C (68-77°F)
- store in a cool dry place away from direct sunlight

Inactive ingredients

Alcohol Denat., Aloe Barbadensis Leaf Extract, Arctium Lappa Root Extract, Arnica Montana Flower Extract, Bis-PEG-10 Dimethicone, Boswellia Carterii Resin Extract, Calendula Officinalis Flower Extract, Camellia Sinensis Leaf Extract, Hydroxyethyl Cetyldimonium Phosphate, Ilex Paraguariensis Leaf Extract, Isopropyl Palmitate, Melissa Officinalis Leaf Extract, PEG-12 Dimethicone, Pentylene Glycol, PPG-24-Glycereth-24, Water

Questions or comments?

1-800-246-3733

Dist. by: RB Health (US), Parsippany, NJ 07054-0224

PRINCIPAL DISPLAY PANEL - 88 mL Bottle Label

CLINICALLY
RECOMMENDED

NDC 59316-991-10

BIOFREEZE®
COOL THE PAIN

FAST
DRY
FOAM

MENTHOL-PAIN
RELIEVING LIQUID

- RUBS IN EASILY
- LIGHTWEIGHT FEEL
- DRIES QUICKLY

3 FL OZ (88 mL)